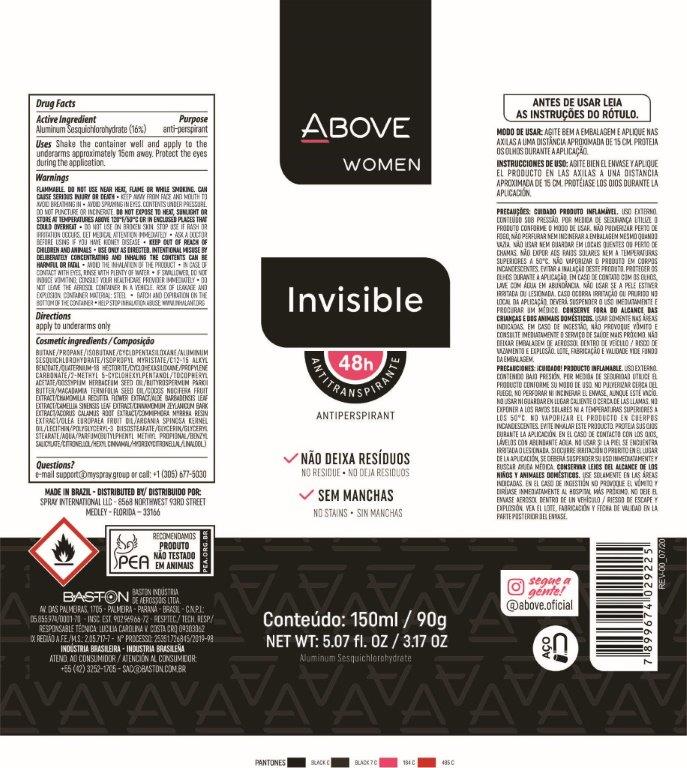 DRUG LABEL: ANTIPERSPIRANT ABOVE INVISIBLE FEMININO
NDC: 73306-1121 | Form: AEROSOL, SPRAY
Manufacturer: BASTON INDUSTRIA DE AEROSSÓIS LTDA
Category: otc | Type: HUMAN OTC DRUG LABEL
Date: 20241009

ACTIVE INGREDIENTS: ALUMINUM SESQUICHLOROHYDRATE 16 g/100 g
INACTIVE INGREDIENTS: ISOPROPYL MYRISTATE; ALOE VERA LEAF; ALKYL (C12-15) BENZOATE; POLYGLYCERYL-3 DIISOSTEARATE; CYCLOMETHICONE 5; LEVANT COTTON SEED; DIMETHICONE; 2-METHYL 5-CYCLOHEXYLPENTANOL; GLYCERIN; PROPYLENE CARBONATE; ARGAN OIL; PROPANE; BUTANE; GREEN TEA LEAF; CINNAMON BARK OIL; .ALPHA.-TOCOPHEROL ACETATE; SHEA BUTTER; WATER; MYRRH OIL; GLYCERYL MONOSTEARATE; CHAMOMILE; ISOBUTANE; DISTEARDIMONIUM HECTORITE; COCONUT; LECITHIN, SOYBEAN; ACORUS CALAMUS ROOT; MACADAMIA OIL

antiperspirant above invisible feminino aerosol